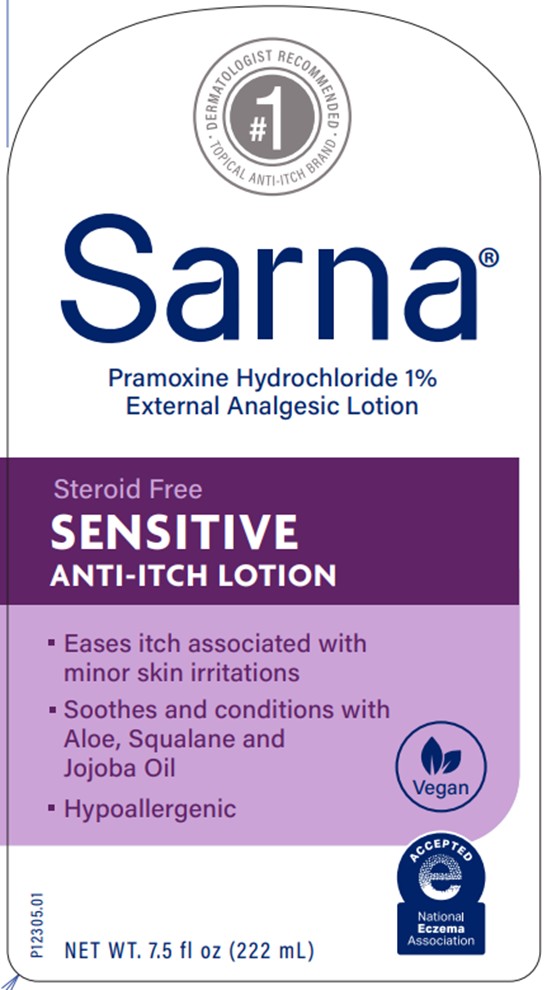 DRUG LABEL: Sarna
NDC: 0316-0230 | Form: LOTION
Manufacturer: Crown Laboratories
Category: otc | Type: HUMAN OTC DRUG LABEL
Date: 20260112

ACTIVE INGREDIENTS: PRAMOXINE HYDROCHLORIDE 10 mg/1 mL
INACTIVE INGREDIENTS: SODIUM HYDROXIDE; BENZYL ALCOHOL; PENTYLENE GLYCOL; SACCHARIDE ISOMERATE; GLYCERYL MONOSTEARATE; ALOE VERA LEAF; ETHYLHEXYLGLYCERIN; SIMMONDSIA CHINENSIS SEED; TOCOPHEROL; WATER; PEG-100 STEARATE; PEG-8 STEARATE; SQUALANE; CAPRYLYL GLYCOL; ISOPROPYL MYRISTATE; PALMITIC ACID; SODIUM CITRATE; CARBOMER HOMOPOLYMER TYPE C; CETYL ALCOHOL; CITRIC ACID MONOHYDRATE; YEAST .BETA.-D-GLUCAN; DIMETHICONE; STEARIC ACID

Sarna Sensitive

Active ingredient

Pramoxine Hydrochloride 1%

Purpose

External analgesic

Uses

- for the temporary relief of pain and itching associated with minor burns, sunburn, minor cuts, scrapes, insect bites, minor skin irritations and rashes due to poison ivy, poison oak, or poison sumac

Warnings

For external use only.

Do not use

- in the eyes
- over large areas of the body
- for prolonged periods

When using this product

- avoid contact with eyes
- if condition worsens, or if symptoms persist for more than 7 days or clear up and occur again within a few days, discontinue use of this product and consult a doctor.

Stop use and ask a doctor if

- redness, irritation, swelling, or pain persists or increases.

Keep out of reach of children.

If swallowed, get medical help or contact a Poison Control Center right away.

Directions

- To open, hold cap and turn pump clockwise.
- Adults and children 2 years of age and older: Apply to affected area not more than 3 to 4 times daily. Children under 2 years of age: do not use, consult a doctor.

Other information

- store at 20°–25°C (68°–77°F) [see USP Controlled Room Temperature]

Inactive ingredients

Aloe Barbadensis Leaf Juice, Benzyl Alcohol, Beta-Glucan, C12-18 Alkanoyl Glycerin/Sebacic Acid Copolymer, Caprylyl Glycol, Carbomer, Cetyl Alcohol, Citric Acid, Dimethicone, Ethylhexylglycerin, Glyceryl Stearate, Isopropyl Myristate, Palmitic Acid, PEG-100 Stearate, PEG-8 Stearate, Pentylene Glycol, Saccharide Isomerate, Simmondsia Chinensis (Jojoba) Seed Oil, Sodium Citrate, Sodium Hydroxide, Squalane, Stearic Acid, Tocopherol, Water

Sarna Sensitive Principal Display Panel

#1 DERMATOLOGIST RECOMMENDED TOPICAL ANTI-ITCH BRAND

Sarna

Pramoxine Hydrochloride 1%

External Analgesic Lotion

Steroid Free

SENSITIVE

ANTI-ITCH LOTION

- Eases itch associated with minor skin irritations
- Soothes and conditions with Aloe, Squalene, and Jojoba Oil
- Hypoallergenic

NET WT. 7.5fl oz (222 ml)

P12305.01